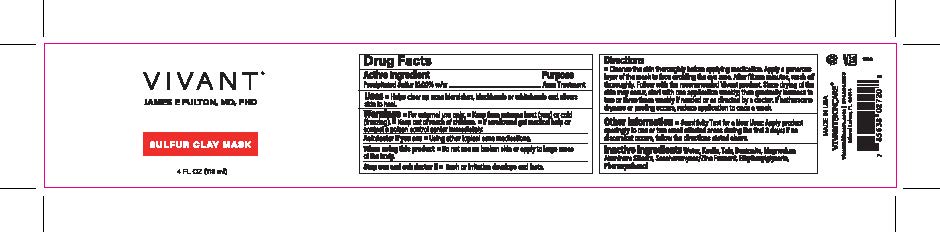 DRUG LABEL: Vivant Sulfur Clay Mask
NDC: 63750-006 | Form: PASTE
Manufacturer: Vivant Pharmaceuticals, LLC
Category: otc | Type: HUMAN OTC DRUG LABEL
Date: 20241105

ACTIVE INGREDIENTS: SULFUR 10 g/100 mL
INACTIVE INGREDIENTS: PHENOXYETHANOL; ETHYLHEXYLGLYCERIN; POLYETHYLENE GLYCOL, UNSPECIFIED; SACCHAROMYCES CEREVISIAE; BENTONITE; KAOLIN; TALC; MAGNESIUM ALUMINUM SILICATE; WATER

Vivant Sulfur Clay Mask

Active ingredient

Precipitated Sulfur, 10%

Purpose

Acne Treatment

Uses

Uses ■ Helps clear up acne blemishes, blackheads or whiteheads and allows skin to heal

Warnings

For external use only

When using this product ■ Do not use on broken skin or apply to large areas of the
body.

Stop use and consult a doctor if

- Rash or irritation develops and last

Keep out of the reach of children.

If swallowed, get medical help or contact a Poison Control Center right away.

Directions

■ Cleanse the skin thoroughly before applying medication. Apply a generous layer of the mask to face avoiding the eye area. After fifteen minutes, wash off thoroughly. Follow with the recommended Vivant product. Since drying of the skin may occur, start with one application weekly; then gradually increase to two or three times weekly if needed or as directed by a doctor. If bothersome
dryness or peeling occurs, reduce application to once a week.

Inactive ingredient

Inactive Ingredients Water, Kaolin, Talc, Bentonite, Magnesium Aluminum Silicate, Saccharomyces/Zinc Ferment, Ethylhexylglycerin, Phenoxyethanol

Questions

1-800-984-8268